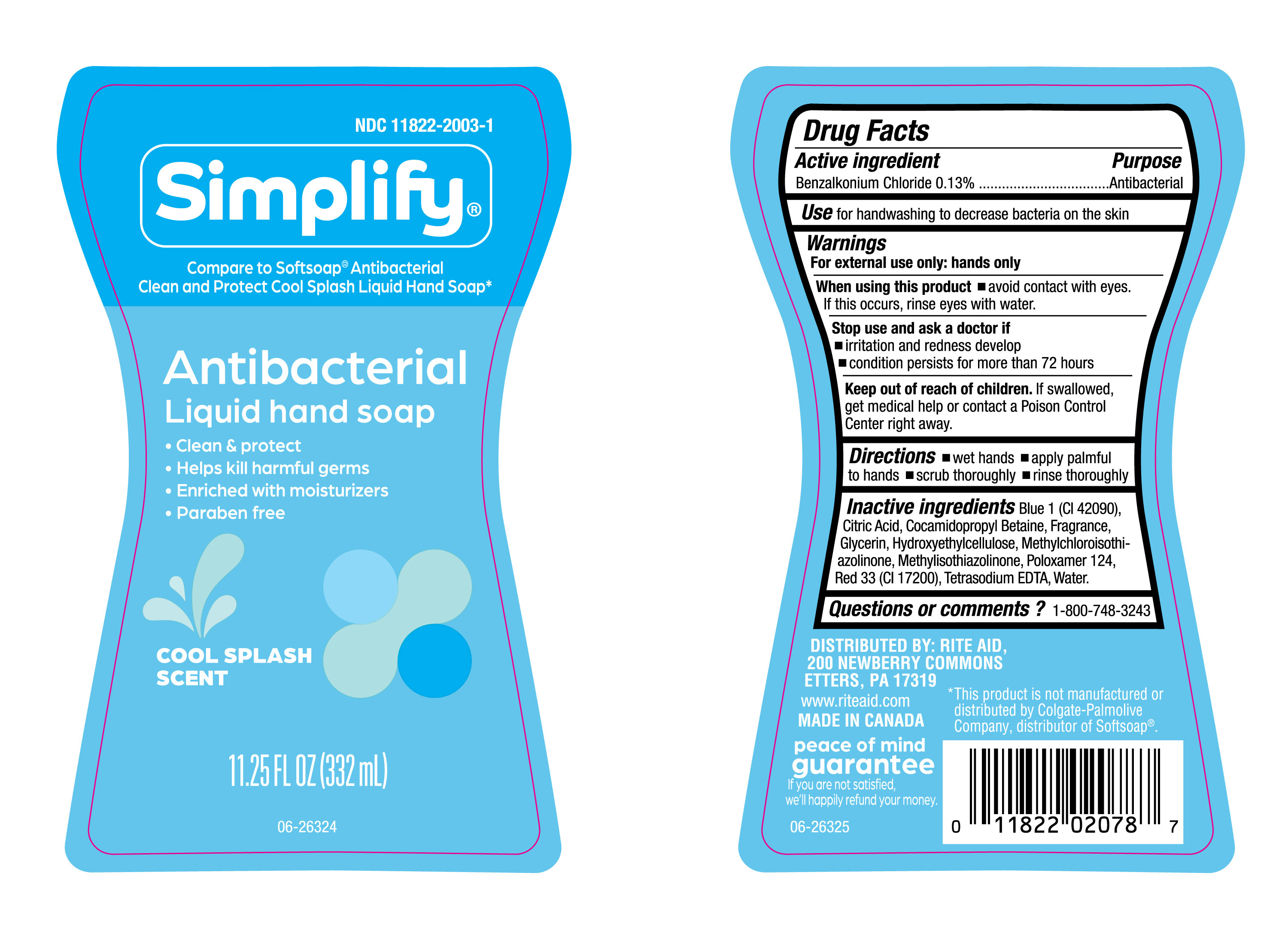 DRUG LABEL: Simplify Clean and Protect Cool Splash LHS
NDC: 11822-2003 | Form: LIQUID
Manufacturer: RITE AID CORPORATION
Category: otc | Type: HUMAN OTC DRUG LABEL
Date: 20250116

ACTIVE INGREDIENTS: BENZALKONIUM CHLORIDE 130 mg/100 mL
INACTIVE INGREDIENTS: FRAGRANCE CLEAN ORC0600327; GLYCERIN; COCAMIDOPROPYL BETAINE; POLOXAMER 124; WATER; HYDROXYETHYLCELLULOSE; BLUE 1; CITRIC ACID; METHYLCHLOROISOTHIAZOLINONE; RED 33; TETRASODIUM EDTA; METHYLISOTHIAZOLINONE

NDC- 11822-2003-1, Simplify Cool Splash Scent Liquid Hand Soap.

Active Ingredient

Benzalkonium Chloride 0.13%

Purpose

Antibacterial

Uses

For Hand washing to decrease bacteria on the skin.

Warnings

For external; use only: hands only.

When using this Product

- Avoid contact with eyes. If this occurs, rinse eyes with water.

Stop use and ask a doctor if

- Irritation andredness develop.
- Condition persists for more than 72 hours.

Keep out of reach of children.

If swallowed, get medical help or contact a Poison Control Center right away.

Directions

- Wet hands.
- Apply palmful to hands.
- Scrub thoroughly.
- rinse thoroughly.

Inactive Ingredients

Blue 1 (CI 42090), Citric Acid, Cocamidopropyl Betaine,Fragrance, Glycerin, Hydroxyethylcellulose, Methylchloroisothiazolinone, Methylisothiazolinone, Poloxamer 124, Red 33 (CI17200), Tetrasodium EDTA, Water.

Questions or comments?

1-800-748-3243.